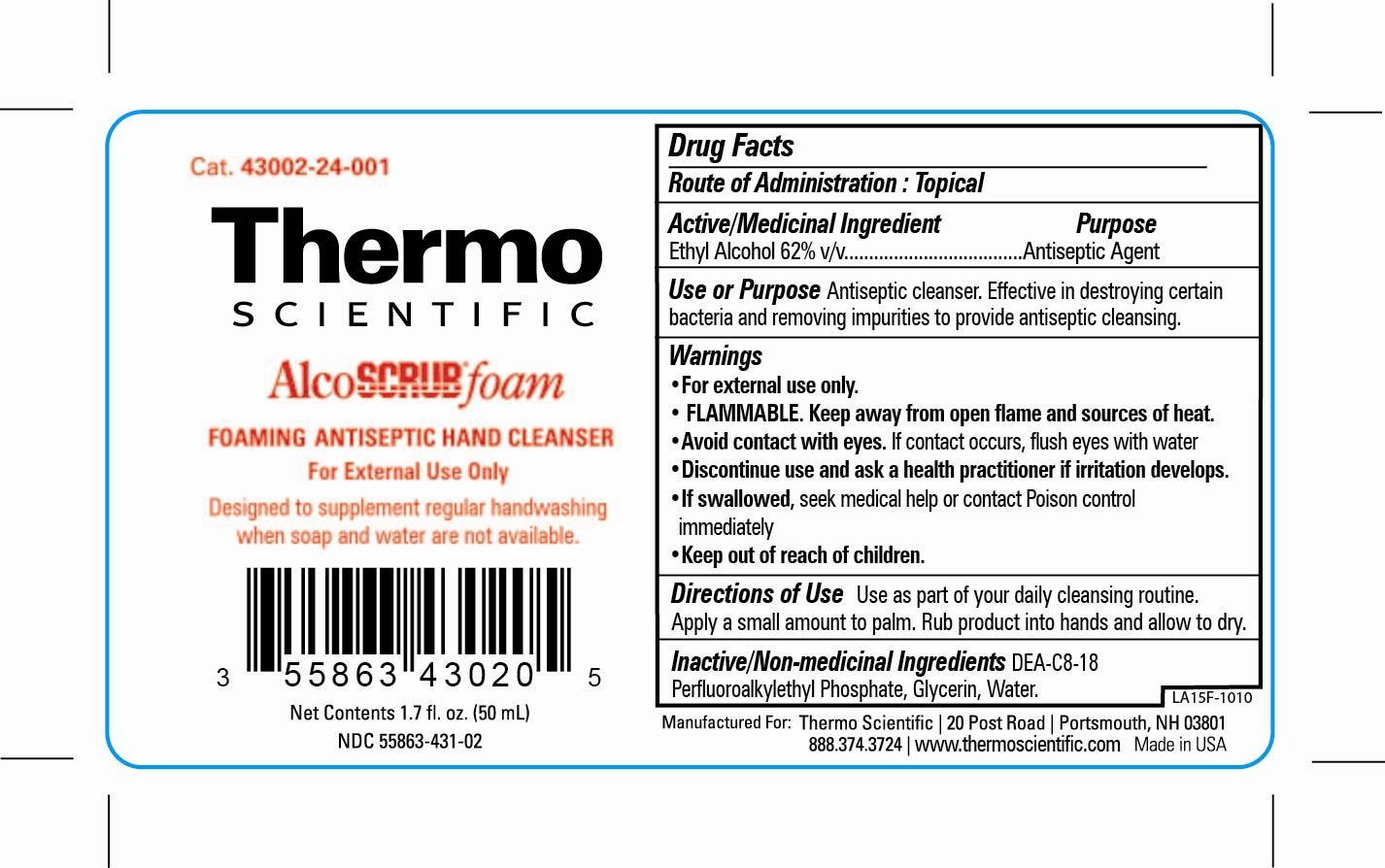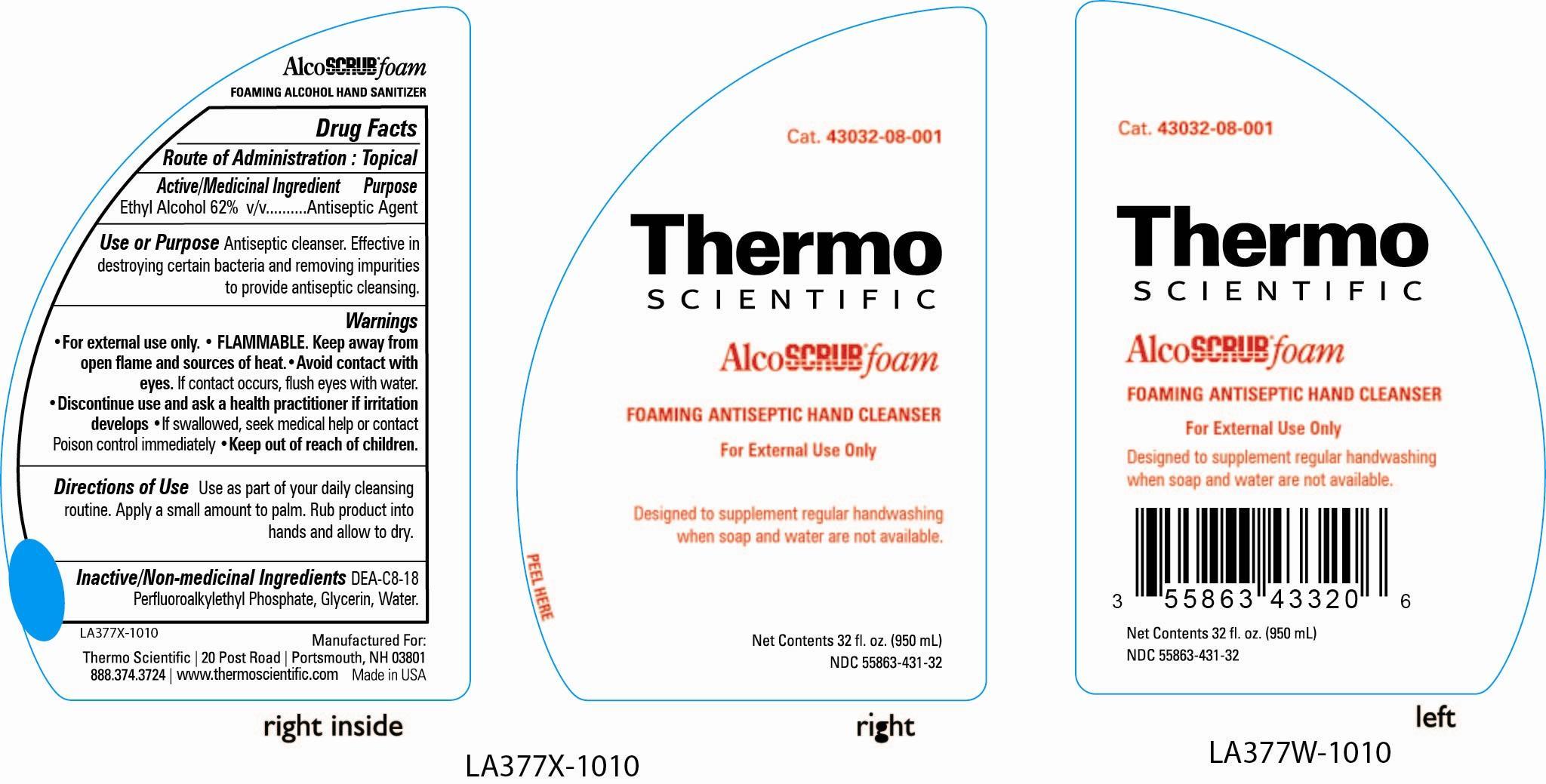 DRUG LABEL: Alcoscrub Foam
NDC: 55863-431 | Form: LIQUID
Manufacturer: Erie Scientific, LLC
Category: otc | Type: HUMAN OTC DRUG LABEL
Date: 20130718

ACTIVE INGREDIENTS: ALCOHOL 1 mL/1 mL
INACTIVE INGREDIENTS: WATER; GLYCERIN; DIETHANOLAMINE BIS(C8-C18 PERFLUOROALKYLETHYL)PHOSPHATE

AlcoScrub Foam

ACTIVE INGREDIENT

Ethyl Alcohol 62% v/v

INACTIVE INGREDIENT

DEA-C8-18 Perfluoroalkylethyl Phosphate, Glycerin, Water

DOSAGE AND ADMINISTRATION

Use as part of your daily cleaning routine. Apply a small amount to palm. Rub product into hands and allow to dry.

PURPOSE

Antiseptic Cleanser. Effective in destroying certain bacteria and removing impurities to provide antiseptic cleansing.

INDICATIONS AND USAGE

Antiseptic cleanser. Use as part of your daily cleaning routine.

Flammable. Keep away from open flame and sources of heat. Avoid contact with eyes.

Discontinue use and ask a health practitioner if irritation develops. If swallowed seek medical help or contact Posion Control immediately. Keep out of reach of children.

KEEP OUT OF REACH OF CHILDREN

If swallowed seek medical help or contact Posion Control immediately.

WARNINGS

For external use only.

Flammable. Keep away from open flame and sources of heat.

Avoid contact with eyes. If contact occurs, flush eyes with water.

Discontinue use and ask a health practitioner if irritation develops.

If swallowed seek medical help or contact Posion Control immediately.

Keep out of reach of children.